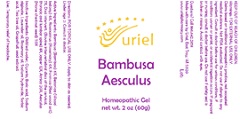 DRUG LABEL: BAMBUSA AESCULUS
NDC: 48951-2003 | Form: GEL
Manufacturer: URIEL PHARMACY INC.
Category: homeopathic | Type: HUMAN OTC DRUG LABEL
Date: 20201218

ACTIVE INGREDIENTS: BAMBUSA VULGARIS WHOLE 6 [hp_X]/1 g; STACHYS OFFICINALIS 6 [hp_X]/1 g; ROSMARINUS OFFICINALIS FLOWERING TOP 6 [hp_X]/1 g; FORMICA RUFA 7 [hp_X]/1 g; BOS TAURUS INTERVERTEBRAL DISC 8 [hp_X]/1 g; SILICON DIOXIDE 12 [hp_X]/1 g; ARNICA MONTANA 20 [hp_X]/1 g; HORSE CHESTNUT 50 [hp_X]/1 g
INACTIVE INGREDIENTS: SORBIC ACID; BORIC ACID; WATER; GLYCERIN; SODIUM ALGINATE; LAVENDER OIL; ROSEMARY OIL; SODIUM HYDROXIDE; CITRUS PARADISI SEED; TEA TREE OIL

Bambusa Aesculus

INDICATIONS AND USAGE

Directions: FOR TOPICAL USE ONLY.

DOSAGE AND ADMINISTRATION

Apply to skin as needed. Under age 2: Consult a doctor.

ACTIVE INGREDIENT

Active Ingredients: Bambusa (Bamboo) 6X, Betonica (Wood betony) 6X, Rosmarinus (Rosemary) 6X, Formica (Red wood ant) 7X, Disci intervert. (Bovine intervertebral discs of the cervical, thoracic and lumbar spine) 8X, Jasper 12X, Arnica 20X, Aesculus (Horse chestnut seed) 50X

INACTIVE INGREDIENT

Inactive Ingredients: Distilled water, Glycerin, Boric acid, Sodium alginate, Lavender oil, Rosemary oil,Sodium hydroxide, Sorbic acid, Tea tree oil, Grapefruit seed extract

PURPOSE

Use: Temporary relief of headache.

KEEP OUT OF REACH OF CHILDREN.

Warnings: FOR EXTERNAL USE ONLY.
Claims based on traditional homeopathic practice, not accepted medical evidence. Not FDA evaluated. Do not use if allergic to any ingredient. Consult a doctor before use for serious conditions, if conditions worsen or persist, or accidental ingestion occurs. If pregnant or nursing, consult a doctor before use. Do not use if safety seal is broken or missing. Avoid contact with eyes.

Questions? Call 866.642.2858
Made with care by Uriel, East Troy, WI 53120
www.urielpharmacy.com

Lot: